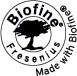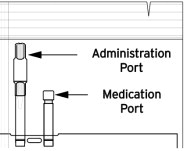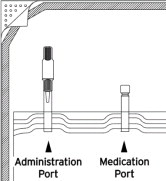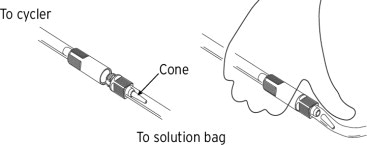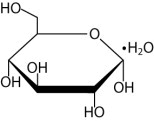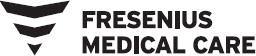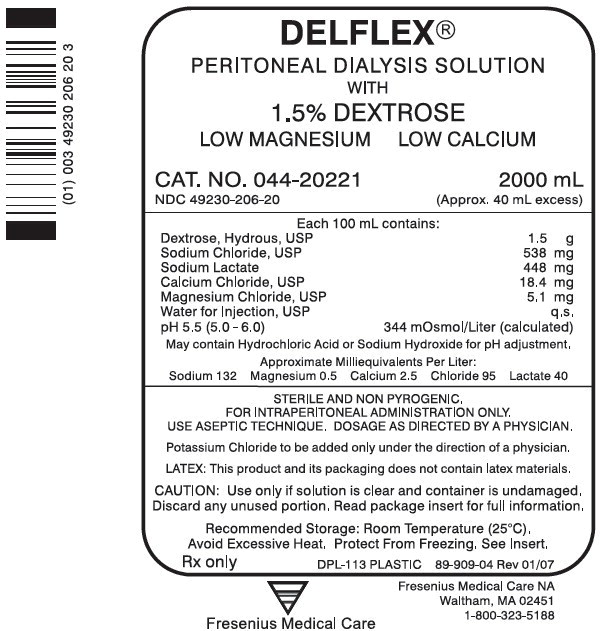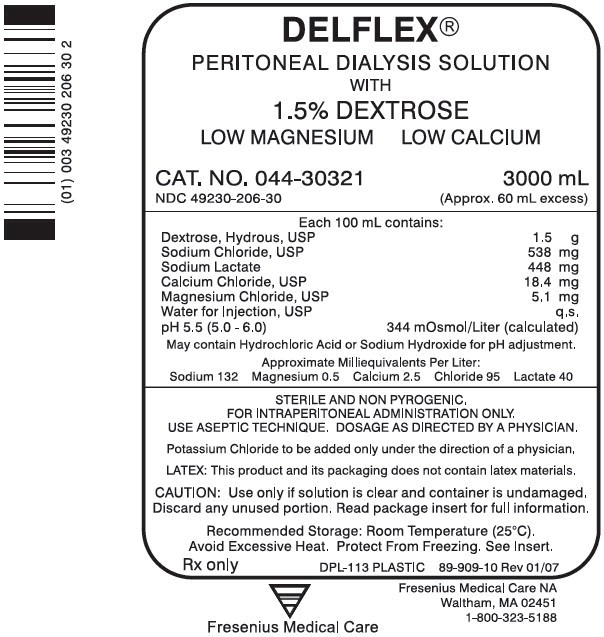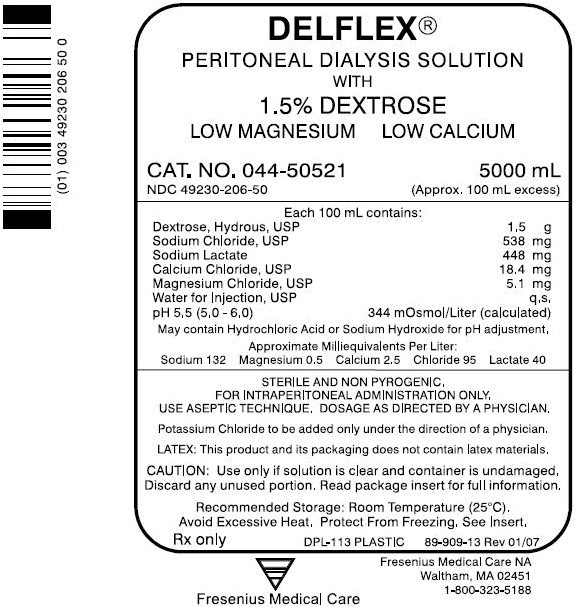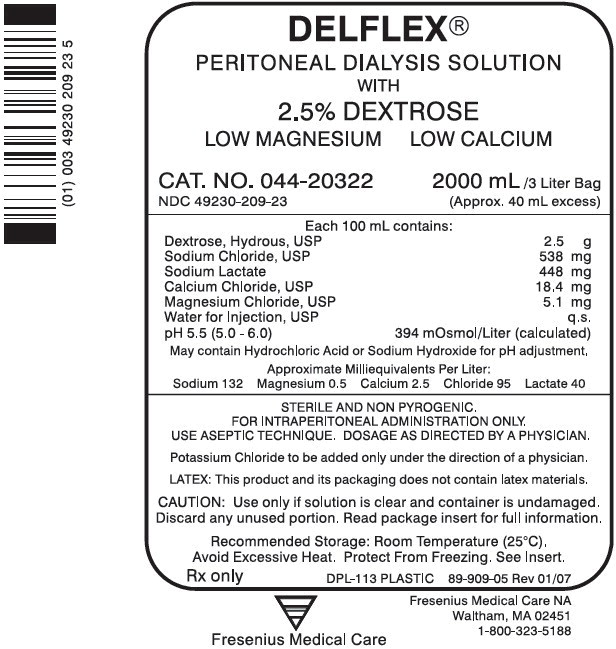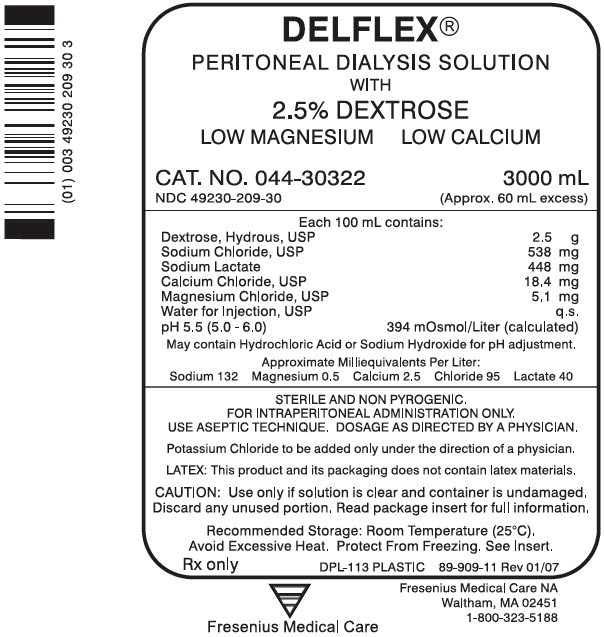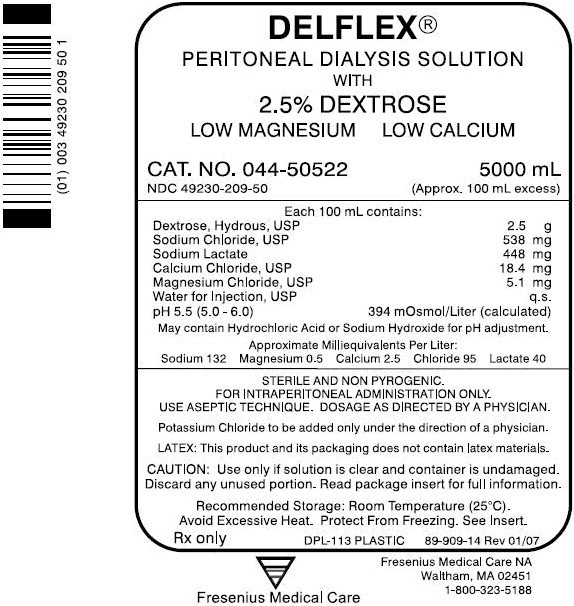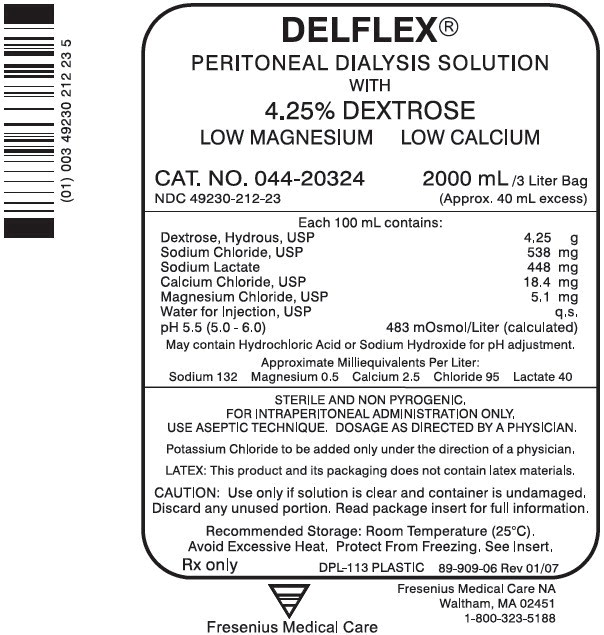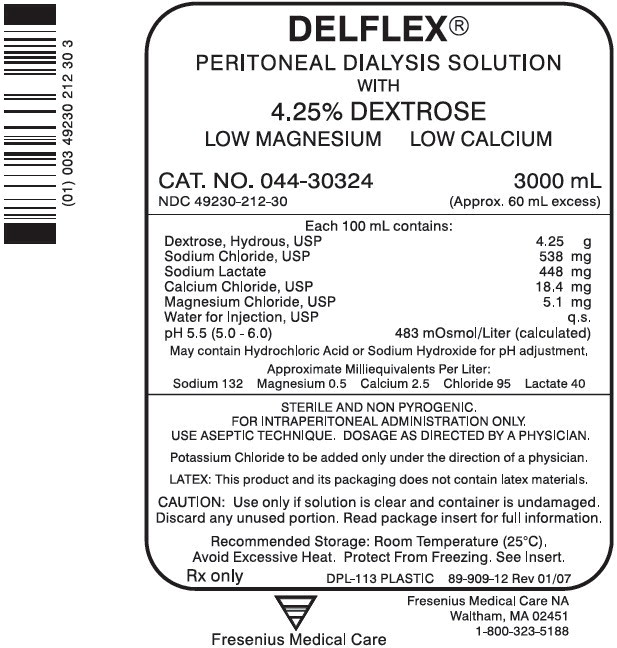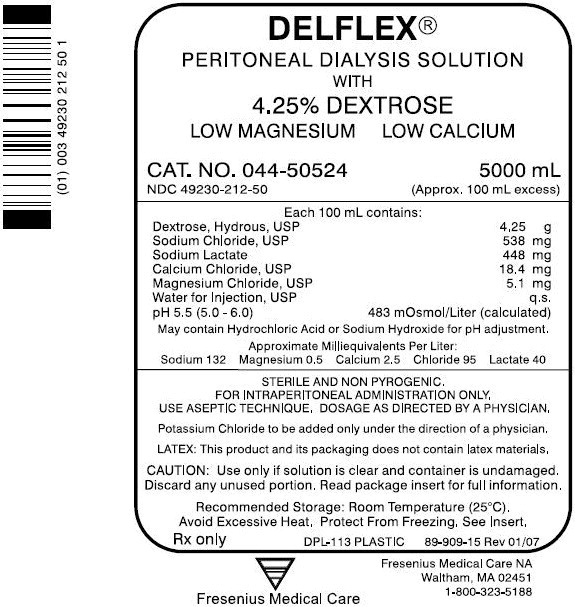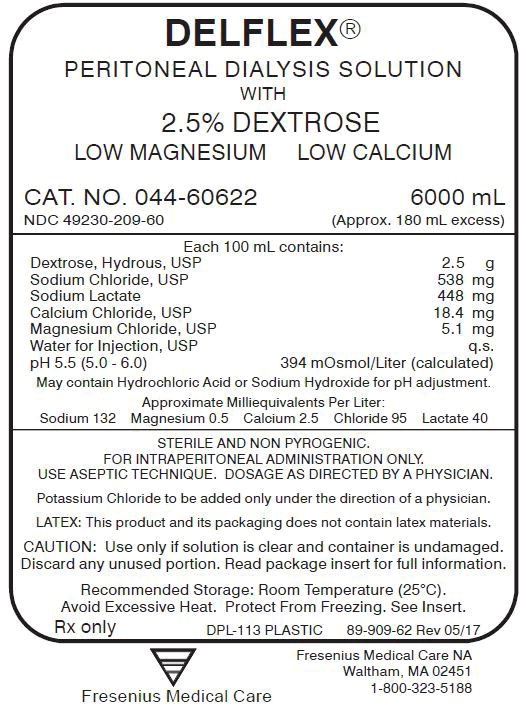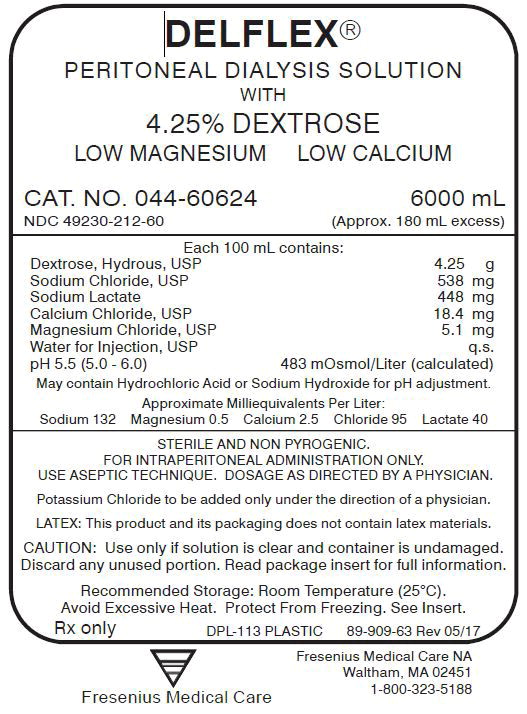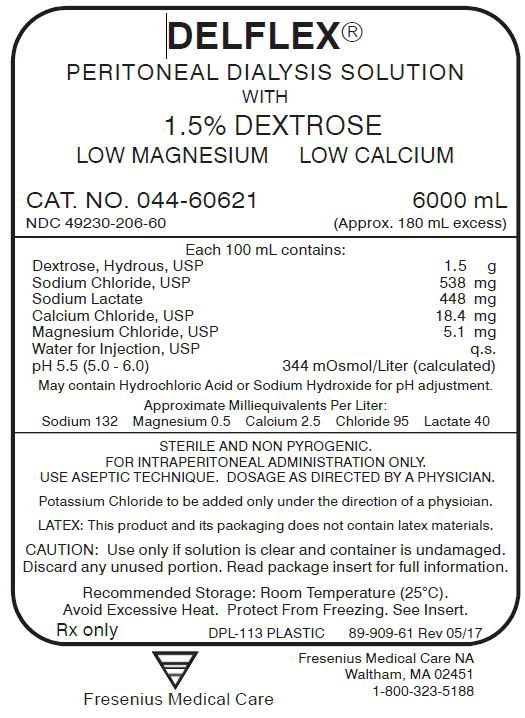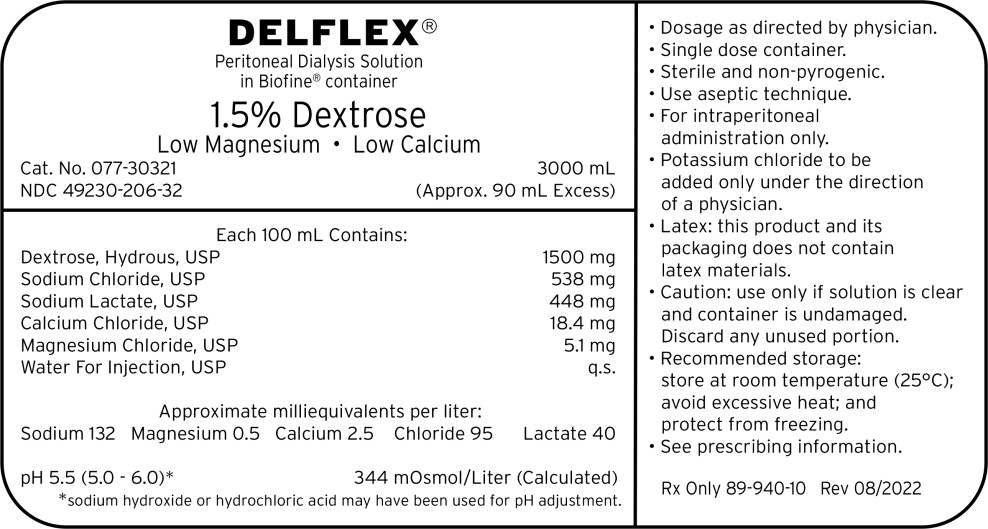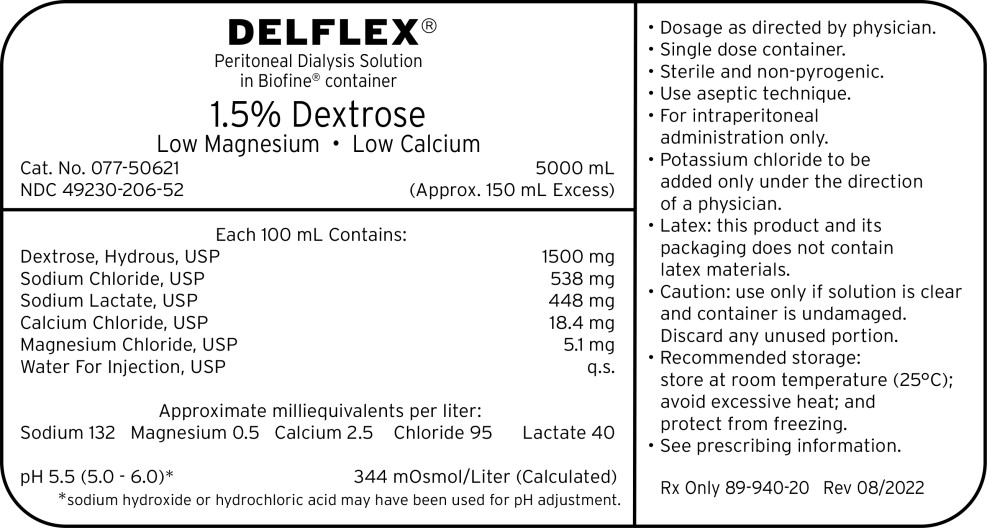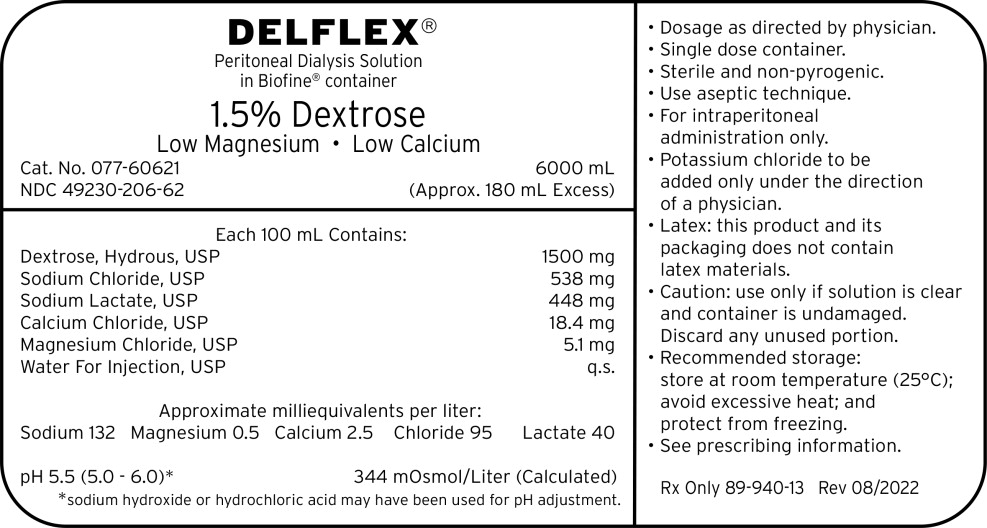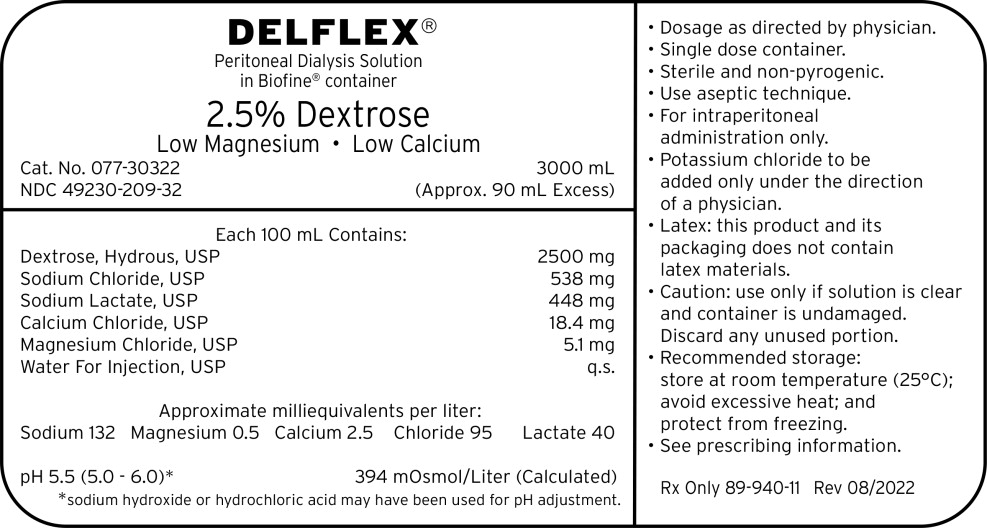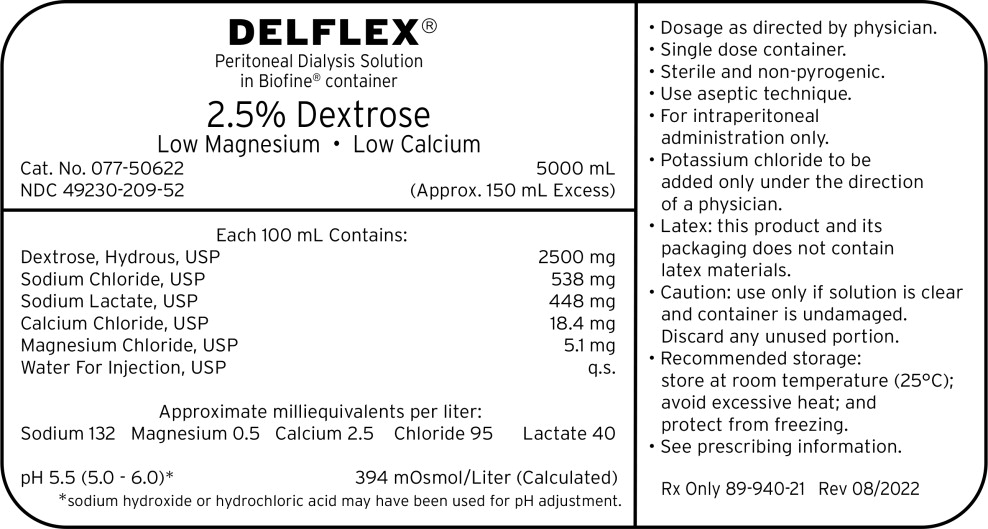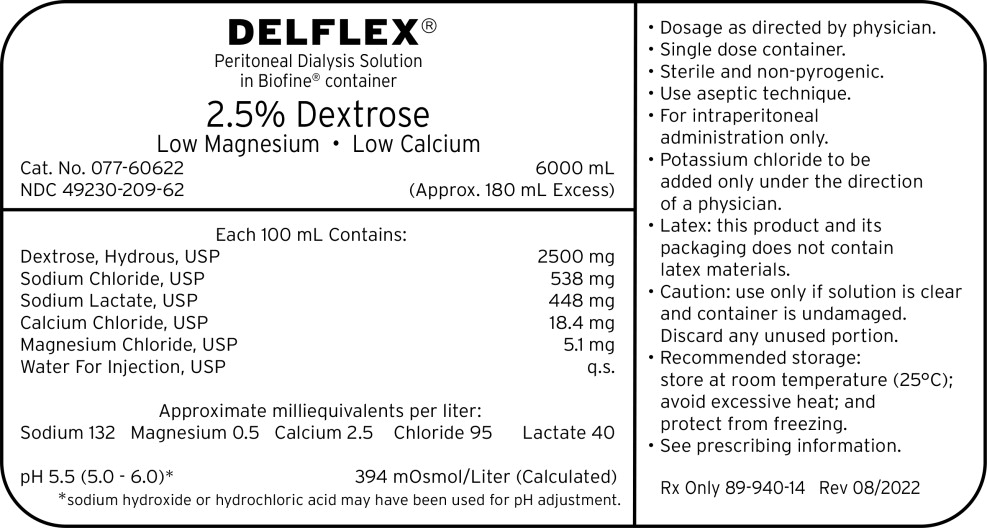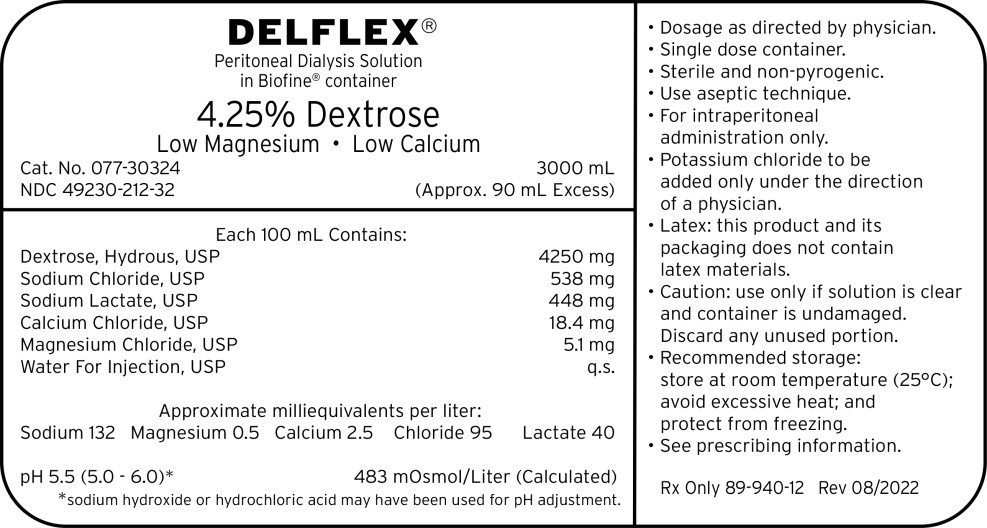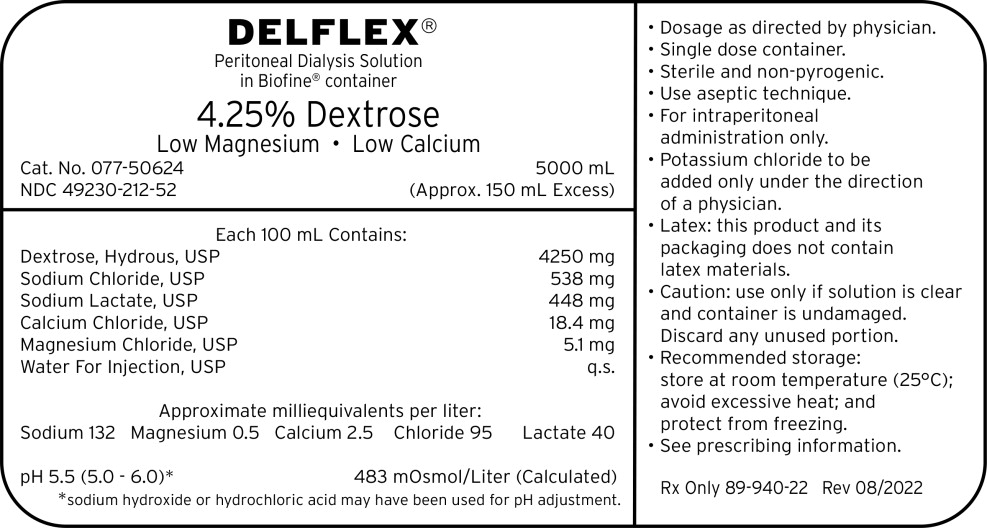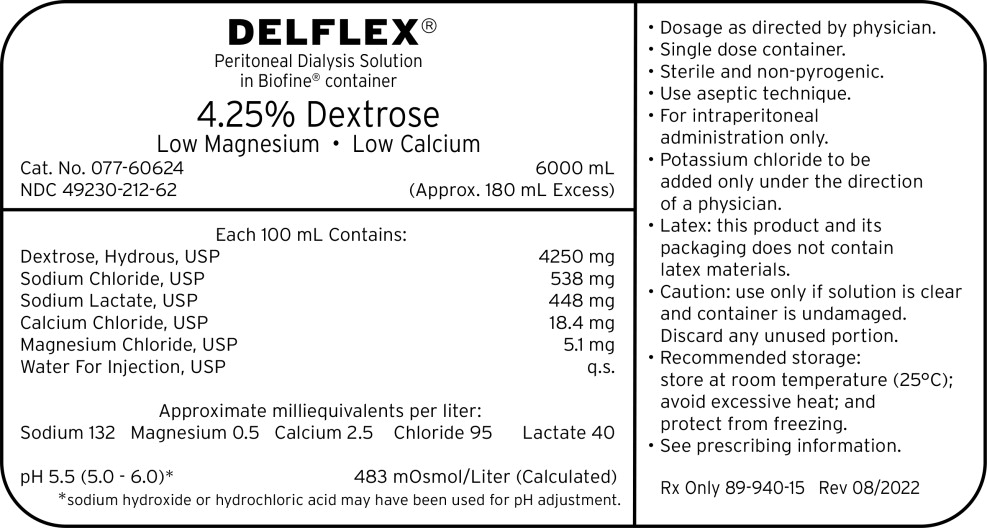 DRUG LABEL: DELFLEX
NDC: 49230-206 | Form: SOLUTION
Manufacturer: Fresenius Medical Care Renal Therapies Group, LLC
Category: prescription | Type: HUMAN PRESCRIPTION DRUG LABEL
Date: 20251123

ACTIVE INGREDIENTS: DEXTROSE MONOHYDRATE
 1.5 g/100 mL; SODIUM CHLORIDE
 538 mg/100 mL; SODIUM LACTATE
 448 mg/100 mL; CALCIUM CHLORIDE
 18.4 mg/100 mL; MAGNESIUM CHLORIDE
 5.08 mg/100 mL
INACTIVE INGREDIENTS: WATER

HIGHLIGHTS OF PRESCRIBING INFORMATION

These highlights do not include all the information needed to use DELFLEX® safely and effectively. See full prescribing information for DELFLEX®
DELFLEX (dextrose) peritoneal dialysis solution
Initial U.S. Approval: 1984
DELFLEX Low Magnesium, Low Calcium (dextrose) peritoneal dialysis solution
Initial U.S. Approval: 1992

1. INDICATIONS AND USAGE

For treatment of chronic kidney failure. (1)

2. DOSAGE AND ADMINISTRATION

For intraperitoneal dialysis only. (2)

3. DOSAGE FORMS AND STRENGTHS

DELFLEX solutions are available in multiple compositions, calculated osmolarity, pH, and ionic concentrations. See full prescribing information for detailed descriptions of each formulation. (3, 11)

4. CONTRAINDICATIONS

None

5. WARNINGS AND PRECAUTIONS

- Monitor patient for electrolyte, fluid, and nutrition imbalances. (5.1)
- Encapsulating Peritonitis Sclerosis (EPS) (5.2)
- Peritonitis: Initiate appropriate antimicrobial therapy (5.2)
- Monitor for Lactic Acidosis in patients at risk. (5.3)

6. ADVERSE REACTIONS

Adverse reactions may include peritonitis, catheter site infection, electrolyte and fluid imbalances, hypovolemia, hypervolemia, hypertension, disequilibrium syndrome, muscle cramping, abdominal pain, abdominal distension, and abdominal discomfort. (6)

To report SUSPECTED ADVERSE REACTIONS, contact Fresenius Medical Care North America at 1-800-323-5188 or FDA at 1-800-FDA-1088 or www.fda.gov/medwatch.

FULL PRESCRIBING INFORMATION

1. INDICATIONS AND USAGE

DELFLEX® is indicated in the treatment of chronic kidney failure in patients being maintained on peritoneal dialysis.

2. DOSAGE AND ADMINISTRATION

2.1 Basic Dosing Information

DELFLEX® is intended for intraperitoneal administration only. Not for intravenous or intra-arterial administration.

The mode of therapy, frequency of treatment, formulation, exchange volume, duration of dwell, and length of dialysis should be selected by the physician responsible for the treatment of the individual patient.

Utilize the peritoneal dialysis solution with lowest level of osmolarity consistent with the fluid removal requirements for that exchange.

Do not store solutions containing additives.

2.2 Administration Instructions

Parenteral drug products should be inspected visually for particulate matter and discoloration prior to administration whenever solution and container permit.

Do not heat in a microwave oven.

Get Ready

1. Clean work surface.
2. Gather supplies:
  - DELFLEX peritoneal dialysis bag(s).
  - Prescribed medication(s), if ordered by your healthcare provider.
  - Mask.
3.
  PVC
  Tear the overwrap from the slit edge down the length of the inner bag to open. | Locate pull tabs on overwrap. Grasping one tab in each hand, pull outward, down the length of the inner bag to open.
  Wipe away any moisture from the solution bags. Some opacity may be observed in the plastic of the bag and/or tubing and is due to moisture absorption during the sterilization process. This is normal and does not affect the solution quality or safety. The opacity will diminish gradually. | Wipe away any moisture from the solution bags.
  Inspect DELFLEX Solution Bag
4. After removing the overwrap, check your DELFLEX solution bag(s) for strength, clarity, amount, leaks, and expiration date. Do not use DELFLEX solution if leaks are found, the solution bag is damaged, and/or the solution is cloudy or discolored, or the product is expired. Color may vary from clear to slightly yellow but does not affect efficacy and may be used.
5. Visually check that the solution bag tubing is free from kinks. If kinks are present, straighten tubing to allow the solution to flow freely.
  Note: Retain DELFLEX peritoneal dialysis bag sample for manufacturer evaluation and notify your healthcare provider if any of the above defects are found.
  Note: DELFLEX peritoneal dialysis solutions utilize the Safe-Lock® Connection System. This unique system consists of two Safe-Lock connectors, one located on the administration port of the bag, and the mating connector is located on the cycler set. The Safe-Lock connectors were designed to reduce the potential risk of touch contamination of the internal connection components.
6. Put on mask. Wash your hands.
7. If you will be adding medications(s):
  - Clean hands (as per facility's protocol)
  - Clean the medication port as instructed by your healthcare provider.
  - Add the medicine(s).
  - Turn the bag upside down several times to mix the medicine(s).
8. To connect the bag(s) to the cycler set, unscrew the protective caps of the administration port and the cycler set solution line connector. Secure these two connectors with a twisting motion to lock in place, so that the cycler set connector is seated over the administration port O-ring to assure a firm and tight fit.
9. After completing Step 8, wait for the cycler prompt to break the administration port cone and initiate solution flow. Do this by placing the thumb firmly on the tube over the cone and pressing towards the outer wall of the tube and away from the bag.
10. Perform your treatment as prescribed.
11. At the end of your treatment, throw away the fluid and used set as instructed by your healthcare provider. In case of cloudiness, save the fluid and the used set and immediately contact your healthcare provider. Dispose of your empty solution bag according to your local recycling program. Empty solution bags may not be recyclable in your area.

2.3 Compatible Medications

Compatible medications can be added via the medication port [see Dosage and Administration (2.2)]. The following medications have demonstrated stability with DELFLEX solutions: cefazolin, ceftazidime, gentamicin, and vancomycin [see Clinical Pharmacology (12.3)] .

3. DOSAGE FORMS AND STRENGTHS

DELFLEX peritoneal dialysis solutions are available in single-dose flexible bags comprised of either polyvinyl chloride (PVC), or a proprietary blend of polyolefins called Biofine®. All DELFLEX peritoneal dialysis solutions have overfills declared on the bag label.

DELFLEX peritoneal dialysis solutions are available in the sizes and formulations shown in Table 1.

Table 1. DELFLEX peritoneal dialysis solution sizes and formulations
 | PVC |  |  |  | Biofine®
 | 2L | 3L | 5L | 6L | 3L | 5L | 6L
DELFLEX Standard with 1.5% Dextrose |  |  | X | X |  | X | X
DELFLEX Standard with 2.5% Dextrose |  |  | X | X |  | X | X
DELFLEX Low Magnesium, Low Calcium with 1.5% Dextrose | X | X | X | X | X | X | X
DELFLEX Low Magnesium, Low Calcium with 2.5% Dextrose | X | X | X | X | X | X | X
DELFLEX Low Magnesium, Low Calcium with 4.25% Dextrose | X | X | X | X | X | X | X

4. CONTRAINDICATIONS

None.

5. WARNINGS AND PRECAUTIONS

5.1 Electrolyte, Fluid and Nutrition Imbalances

Peritoneal dialysis may affect a patient's protein, water-soluble vitamin, potassium, sodium, chloride, bicarbonate, and magnesium levels and volume status. Monitor electrolytes and blood chemistry periodically and take appropriate clinical action.

Potassium is omitted from DELFLEX solutions because dialysis may be performed to correct hyperkalemia. In situations where there is a normal serum potassium level or hypokalemia, the addition of potassium chloride (up to a concentration of 4 mEq/L) may be indicated to prevent severe hypokalemia.

To avoid the risk of severe dehydration or hypovolemia and to minimize the loss of protein, it is advisable to select the peritoneal dialysis solution with lowest level of osmolarity consistent with the fluid removal requirements for that exchange.

Significant loss of protein, amino acids and water-soluble vitamins may occur during peritoneal dialysis. Replacement therapy should be provided as necessary.

5.2 Peritonitis and Encapsulating Peritoneal Sclerosis

Infectious and aseptic peritonitis has been associated with peritoneal dialysis therapy. Following DELFLEX use, inspect the drained fluid for the presence of fibrin or cloudiness, which may indicate the presence of peritonitis. Improper clamping or priming sequence may result in infusion of air into the peritoneal cavity, which may result in abdominal pain and/or peritonitis. If peritonitis occurs, treat with appropriate therapy.

Encapsulating peritoneal sclerosis (EPS), sometimes fatal, is a complication of peritoneal dialysis therapy.

5.3 Lactic Acidosis

Monitor patients with conditions known to increase the risk of lactic acidosis [e.g., severe hypotension or sepsis that can be associated with acute kidney failure, inborn errors of metabolism, treatment with drugs such as nucleoside/nucleotide reverse transcriptase inhibitors (NRTIs)] for lactic acidosis before the start of treatment and during treatment with DELFLEX.

Solutions containing the lactate ion should be used with great care in patients with metabolic or respiratory alkalosis. Lactate should be administered with great care in those conditions in which there is an increased level or an impaired utilization of this ion, such as severe hepatic insufficiency.

5.4 Over Infusion

Over infusion of peritoneal dialysis solution volume into the peritoneal cavity may be characterized by abdominal distention, feeling of fullness and/or shortness of breath. Drain the peritoneal dialysis solution from the peritoneal cavity to treat over infusion.

6. ADVERSE REACTIONS

Solution related adverse reactions may include peritonitis, catheter site infection, electrolyte and fluid imbalances, hypovolemia, hypervolemia, hypertension, hypotension, disequilibrium syndrome, muscle cramping, abdominal pain, abdominal distension, and abdominal discomfort.

8. USE IN SPECIFIC POPULATIONS

8.1 Pregnancy

Risk Summary

DELFLEX solutions consist of electrolytes, lactate, and bicarbonate at physiological levels, and glucose to facilitate ultrafiltration. While there are no adequate and well controlled studies in pregnant women, appropriate administration of DELFLEX with monitoring of fluid, electrolyte, acid-base and glucose balance, is not expected to cause fetal harm. Animal reproduction studies have not been conducted with DELFLEX.

The estimated background risk of major birth defects and miscarriage for the indicated population are unknown. All pregnancies have a background risk of birth defect, loss or other adverse outcomes. In the U.S. general population, the estimated background risk of major birth defects and miscarriage in clinically recognized pregnancies is 2 to 4% and 15 to 20%, respectively.

8.2 Lactation

Risk Summary

The components of DELFLEX solutions are excreted in human milk. Appropriate administration of DELFEX solutions with monitoring of fluid, electrolyte, acid-base and glucose balance, is not expected to harm a nursing infant.

8.4 Pediatric Use

Safety and effectiveness in pediatric patients have not been established.

11. DESCRIPTION

The DELFLEX® peritoneal dialysis solutions (standard and low magnesium/low calcium) are sterile, non-pyrogenic formulations of dextrose and electrolytes in water for injection, USP, for use in peritoneal dialysis. These solutions do not contain antimicrobial agents or additional buffers. Composition, calculated osmolarity, pH, and ionic concentrations are shown in Table 2.

Table 2. Composition, calculated osmolarity, pH and ionic concentration
 | Composition/100mL |  |  |  |  | Total Osmolarity (mOsmoL/L) (calc) | pH (5.0 - 6.0) | Ionic Concentration (mEq/L)
 | Dextrose Hydrous, USP (C6H12O6⋅H2O) | Sodium Chloride. USP (NaCI) | Sodium Lactate (C3H5NaO3) | Calcium Chloride, USP (CaCl2⋅2H2O) | Magnesium Chloride, USP (MgCl2-6H20) | Total Osmolarity (mOsmoL/L) (calc) | pH (5.0 - 6.0) | Sodium | Calcium | Magnesium | Chloride | Lactate
DELFLEX Standard with 1.5% Dextrose | 1.5 g | 567 mg | 392 mg | 25.7 mg | 15.2 mg | 347 | 5.5 | 132 | 3.5 | 1.5 | 102 | 35
DELFLEX Standard with 2.5% Dextrose | 2.5 g | 567 mg | 392 mg | 25.7 mg | 15.2 mg | 398 | 5.5 | 132 | 3.5 | 1.5 | 102 | 35
DELFLEX Low Magnesium, Low Calcium with 1.5% Dextrose | 1.5 g | 538 mg | 448 mg | 18.4 mg | 5.08 mg | 344 | 5.5 | 132 | 2.5 | 0.5 | 95 | 40
DELFLEX Low Magnesium, Low Calcium with 2.5% Dextrose | 2.5 g | 538 mg | 448 mg | 18.4 mg | 5.08 mg | 394 | 5.5 | 132 | 2.5 | 0.5 | 95 | 40
DELFLEX Low Magnesium, Low Calcium with 4.25% Dextrose | 4.25g | 538 mg | 448 mg | 18.4 mg | 5.08 mg | 483 | 5.5 | 132 | 2.5 | 0.5 | 95 | 40

Dextrose, USP, is chemically designated D-glucose monohydrate (C6H12O6•H2O) a hexose sugar freely soluble in water. The structural formula is shown here:

Calcium chloride, USP, is chemically designated calcium chloride dihydrate (CaCl2•2H2O) white fragments or granules freely soluble in water.

Magnesium chloride, USP, is chemically designated magnesium chloride hexahydrate (MgCl2 •6H2O) colorless flakes or crystals very soluble in water.

Sodium lactate solution, USP, is chemically designated (CH3CH(OH)COONa), a 60% aqueous solution miscible in water.

Sodium chloride, USP, is chemically designated (NaCl), a white, crystalline compound freely soluble in water.

Water for injection, USP, is chemically designated (H2O).

Hydrochloric Acid or Sodium Hydroxide may be added for pH adjustment. pH is 5.5 ± 0.5.

Exposure to temperatures above 25°C (77°F) during transport and storage will lead to minor losses in moisture content. Higher temperatures lead to greater losses. It is unlikely that these minor losses will lead to clinically significant changes within the expiration period. Since the inner bag is compounded from flexible plastic, water may permeate from the inner bag into the overwrap in quantities insufficient to affect the solution significantly. Solutions in contact with the plastic inner bag can cause certain chemical components of the bag to leach out in very small amounts; however, the safety of the plastic formulation is supported by biological tests for plastic containers.

12. CLINICAL PHARMACOLOGY

12.1 Mechanism of Action

DELFLEX peritoneal dialysis solutions are hypertonic peritoneal dialysis solutions containing dextrose, a monosaccharide, as the primary osmotic agent. An osmotic gradient must be created between the peritoneal membrane and the dialysis solution in order for ultrafiltration to occur. The hypertonic concentration of glucose in DELFLEX solutions exert an osmotic pressure across the peritoneal membrane resulting in transcapillary ultrafiltration. Like other peritoneal dialysis solutions, DELFLEX solutions contain electrolytes to facilitate the correction of acid-base and electrolyte abnormalities. DELFLEX solutions contain a buffer, lactate, to help normalize acid-base abnormalities.

12.3 Pharmacokinetics

Absorption

Glucose can be rapidly absorbed from the peritoneal cavity by diffusion and appears quickly in the circulation due to the high glucose concentration gradient between DELFLEX solutions compared to blood capillary glucose level. Absorption per unit time will be the highest at the start of an exchange and decreases over time. The rate of glucose absorption will be dependent upon the transport characteristics of the patient's peritoneal membrane as determined by a peritoneal equilibration test (PET). Glucose absorption will also depend upon the concentration of glucose used for the exchange and the length of the dwell. Transport of other molecules will be dependent upon the molecular size of the solute, the concentration gradient, and the effective peritoneal surface area as determined by the PET.

Metabolism and Elimination

Glucose is metabolized by normal cellular pathways (i.e., glycolysis). Metabolism of lactate occurs in the liver and results in the generation of the bicarbonate. Glucose not absorbed during PD exchange procedure is removed by drainage of the PD solution from the peritoneal cavity.

Drug Interaction Studies

Antibiotics

No formal clinical drug interaction studies have been performed. In vitro studies of the following medications have demonstrated stability with DELFLEX solutions: cefazolin, ceftazidime, gentamicin, and vancomycin.

13. NONCLINICAL TOXICOLOGY

13.1 Carcinogenesis, Mutagenesis, Impairment of Fertility

Long term animal studies with DELFLEX peritoneal dialysis solutions have not been performed to evaluate the carcinogenic potential, mutagenic potential or effect on fertility.

16. HOW SUPPLIED/STORAGE AND HANDLING

DELFLEX peritoneal dialysis solutions are available in the sizes and formulations shown in Table 1 [see Dosage Forms and Strengths (3)] .

Table 3. DELFLEX peritoneal dialysis NDC designations
 | PVC |  |  |  | Biofine®
 | 2L | 3L | 5L | 6L | 3L | 5L | 6L
Standard 1.5% Dextrose |  |  | 49230- 188-50 | 49230- 188-60 |  | 49230- 188-52 | 49230- 188-62
Standard 2.5% Dextrose |  |  | 49230- 191-50 | 49230- 191-60 |  | 49230- 191-52 | 49230- 191-62
Low Mg/Low Ca 1.5% Dextrose | 49230- 206-20 | 49230- 206-30 | 49230- 206-50 | 49230- 206-60 | 49230- 206-32 | 49230- 206-52 | 49230- 206-62
Low Mg/Low Ca 2.5% Dextrose | 49230- 209-23 | 49230- 209-30 | 49230- 209-50 | 49230- 209-60 | 49230- 209-32 | 49230- 209-52 | 49230- 209-62
Low Mg/Low Ca 4.25% Dextrose | 49230- 212-23 | 49230- 212-30 | 49230- 212-50 | 49230- 212-60 | 49230- 212-32 | 49230- 212-52 | 49230- 212-62

Store at 20°C to 25°C (68°F to 77°F); excursions permitted between 15°C and 30°C (between 59°F and 86°F). See USP Controlled Room Temperature. Brief exposure to temperatures up to 40°C (104°F) may be tolerated provided the mean kinetic temperature does not exceed 25°C (77°F); however, such exposure should be minimized.

Keep DELFLEX and all medicines out of the reach of children.

17. PATIENT COUNSELING INFORMATION

Aseptic technique must be used throughout the procedure and at its termination in order to reduce the possibility of infection.

The solution bag should remain in the carton and the overwrap intact until time of use.

Use only after checking for strength, clarity, amount, leaks, and expiration date.

Advise patients that DELFLEX peritoneal dialysis solution should not be heated in a microwave oven.

Care should be taken to ensure that there is not any leakage around the catheter, since if not controlled, the leakage can create edema from subcutaneous infiltration of the dialysis solution. The leakage will also create an inaccurate fluid balance measurement. If any leakage is identified, advise the patient not to proceed with infusion and notify your physician.

Fresenius Medical Care North America
920 Winter Street
Waltham, MA 02451
1-800-323-5188

© 2020, 2022 Fresenius Medical Care. All Rights Reserved. Fresenius Medical Care, triangle logo, DELFLEX, Safe-Lock, Biofine are trademarks of Fresenius Medical Care Holding, Inc. or affiliated companies.

PACKAGE LABEL

Principal Display Panel – 1.5% Dextrose 2000 mL Bag Label

DELFLEX®

PERITONEAL DIALYSIS SOLUTION
WITH
1.5% DEXTROSE

LOW MAGNESIUM • LOW CALCIUM

CAT. NO. 044-20221

NDC 49230-206-20

2000 mL
(Approx. 90 mL excess)

PACKAGE LABEL

Principal Display Panel – 1.5% Dextrose 3000 mL Bag Label

DELFLEX®

PERITONEAL DIALYSIS SOLUTION
WITH
1.5% DEXTROSE

LOW MAGNESIUM • LOW CALCIUM

CAT. NO. 044-30321

NDC 49230-206-30

3000 mL
(Approx. 60 mL excess)

PACKAGE LABEL

Principal Display Panel – 1.5% Dextrose 5000 mL Bag Label

DELFLEX®

PERITONEAL DIALYSIS SOLUTION
WITH
1.5% DEXTROSE

LOW MAGNESIUM • LOW CALCIUM

CAT. NO. 044-50521

NDC 49230-206-50

5000 mL
(Approx. 100 mL excess)

PACKAGE LABEL

Principal Display Panel – 2.5% Dextrose 2000 mL Bag Label

DELFLEX®

PERITONEAL DIALYSIS SOLUTION
WITH
2.5% DEXTROSE

LOW MAGNESIUM • LOW CALCIUM

CAT. NO. 044-20322

NDC 49230-209-23

2000 mL/3 Liter Bag
(Approx. 40 mL excess)

PACKAGE LABEL

Principal Display Panel – 2.5% Dextrose 3000 mL Bag Label

DELFLEX®

PERITONEAL DIALYSIS SOLUTION
WITH
2.5% DEXTROSE

LOW MAGNESIUM • LOW CALCIUM

CAT. NO. 044-30322

NDC 49230-209-30

3000 mL
(Approx. 60 mL excess)

PACKAGE LABEL

Principal Display Panel – 2.5% Dextrose 5000 mL Bag Label

DELFLEX®

PERITONEAL DIALYSIS SOLUTION
WITH
2.5% DEXTROSE

LOW MAGNESIUM • LOW CALCIUM

CAT. NO. 044-50522

NDC 49230-209-50

5000 mL
(Approx. 100 mL excess)

PACKAGE LABEL

Principal Display Panel – 4.25% Dextrose 2000 mL Bag Label

DELFLEX®

PERITONEAL DIALYSIS SOLUTION
WITH
4.25% DEXTROSE

LOW MAGNESIUM • LOW CALCIUM

CAT. NO. 044-20324

NDC 49230-212-23

2000 mL/3 Liter Bag
(Approx. 40 mL excess)

PACKAGE LABEL

Principal Display Panel – 4.25% Dextrose 3000 mL Bag Label

DELFLEX®

PERITONEAL DIALYSIS SOLUTION
WITH
4.25% DEXTROSE

LOW MAGNESIUM • LOW CALCIUM

CAT. NO. 044-30324

NDC 49230-212-30

3000 mL
(Approx. 60 mL excess)

PACKAGE LABEL

Principal Display Panel – 4.25% Dextrose 5000 mL Bag Label

DELFLEX®

PERITONEAL DIALYSIS SOLUTION
WITH
4.25% DEXTROSE

LOW MAGNESIUM • LOW CALCIUM

CAT. NO. 044-50524

NDC 49230-212-50

5000 mL
(Approx. 100 mL excess)

PACKAGE LABEL

Principal Display Panel – 2.5% Dextrose 6000 mL Bag Label

DELFLEX®

PERITONEAL DIALYSIS SOLUTION
WITH
2.5% DEXTROSE

LOW MAGNESIUM • LOW CALCIUM

CAT. NO. 044-60622

NDC 49230-209-60

6000 mL
(Approx. 180 mL excess)

PACKAGE LABEL

Principal Display Panel – 4.25% Dextrose 6000 mL Bag Label

DELFLEX®

PERITONEAL DIALYSIS SOLUTION
WITH
4.25% DEXTROSE

LOW MAGNESIUM • LOW CALCIUM

CAT. NO. 044-60624

NDC 49230-212-60

6000 mL
(Approx. 180 mL excess)

PACKAGE LABEL

Principal Display Panel – 1.5% Dextrose 6000 mL Bag Label

DELFLEX®

PERITONEAL DIALYSIS SOLUTION
WITH
1.5% DEXTROSE

LOW MAGNESIUM • LOW CALCIUM

CAT. NO. 044-60621

NDC 49230-206-60

6000 mL
(Approx. 180 mL excess)

PACKAGE LABEL

Principal Display Panel – 1.5% Dextrose 3000 mL Bag Label

DELFLEX®

Peritoneal Dialysis Solution
in Biofine® container

1.5% Dextrose

Low Magnesium • Low Calcium

Cat. No. 077-30321

NDC 49230-206-32

3000 mL
(Approx. 90 mL Excess)

PACKAGE LABEL

Principal Display Panel – 1.5% Dextrose 5000 mL Bag Label

DELFLEX®

Peritoneal Dialysis Solution
in Biofine® container

1.5% Dextrose

Low Magnesium • Low Calcium

Cat. No. 077-50621

NDC 49230-206-52

5000 mL
(Approx. 150 mL Excess)

PACKAGE LABEL

Principal Display Panel – 1.5% Dextrose 6000 mL Bag Label

DELFLEX®

Peritoneal Dialysis Solution
in Biofine® container

1.5% Dextrose

Low Magnesium • Low Calcium

Cat. No. 077-60621

NDC 49230-206-62

6000 mL
(Approx. 180 mL Excess)

PACKAGE LABEL

Principal Display Panel – 2.5% Dextrose 3000 mL Bag Label

DELFLEX®

Peritoneal Dialysis Solution
in Biofine® container

2.5% Dextrose

Low Magnesium • Low Calcium

Cat. No. 077-30322

NDC 49230-209-32

3000 mL
(Approx. 90 mL Excess)

PACKAGE LABEL

Principal Display Panel – 2.5% Dextrose 5000 mL Bag Label

DELFLEX®

Peritoneal Dialysis Solution
in Biofine® container

2.5% Dextrose

Low Magnesium • Low Calcium

Cat. No. 077-50622

NDC 49230-209-52

5000 mL
(Approx. 150 mL Excess)

PACKAGE LABEL

Principal Display Panel – 2.5% Dextrose 6000 mL Bag Label

DELFLEX®

Peritoneal Dialysis Solution
in Biofine® container

2.5% Dextrose

Low Magnesium • Low Calcium

Cat. No. 077-60622

NDC 49230-209-62

6000 mL
(Approx. 180 mL Excess)

PACKAGE LABEL

Principal Display Panel – 4.25% Dextrose 3000 mL Bag Label

DELFLEX®

Peritoneal Dialysis Solution
in Biofine® container

4.25% Dextrose

Low Magnesium • Low Calcium

Cat. No. 077-30324

NDC 49230-212-32

3000 mL
(Approx. 90 mL Excess)

PACKAGE LABEL

Principal Display Panel – 4.25% Dextrose 5000 mL Bag Label

DELFLEX®

Peritoneal Dialysis Solution
in Biofine® container

4.25% Dextrose

Low Magnesium • Low Calcium

Cat. No. 077-50624

NDC 49230-212-52

5000 mL
(Approx. 150 mL Excess)

PACKAGE LABEL

Principal Display Panel – 4.25% Dextrose 6000 mL Bag Label

DELFLEX®

Peritoneal Dialysis Solution
in Biofine® container

4.25% Dextrose

Low Magnesium • Low Calcium

Cat. No. 077-60624

NDC 49230-212-62

6000 mL
(Approx. 180 mL Excess)